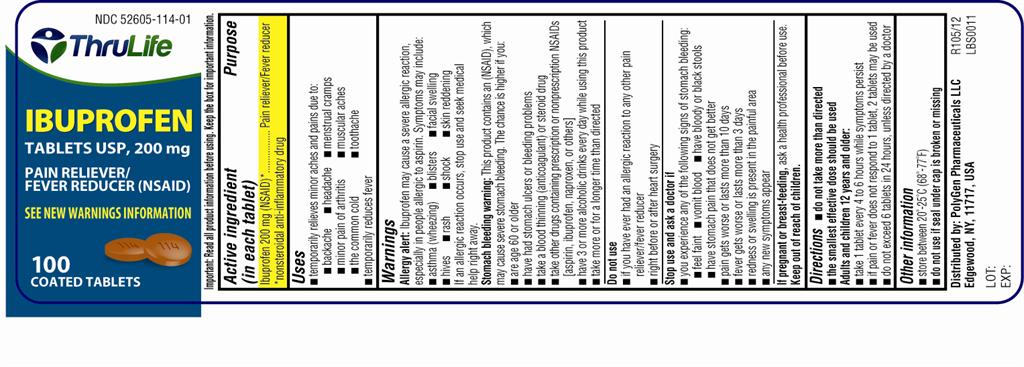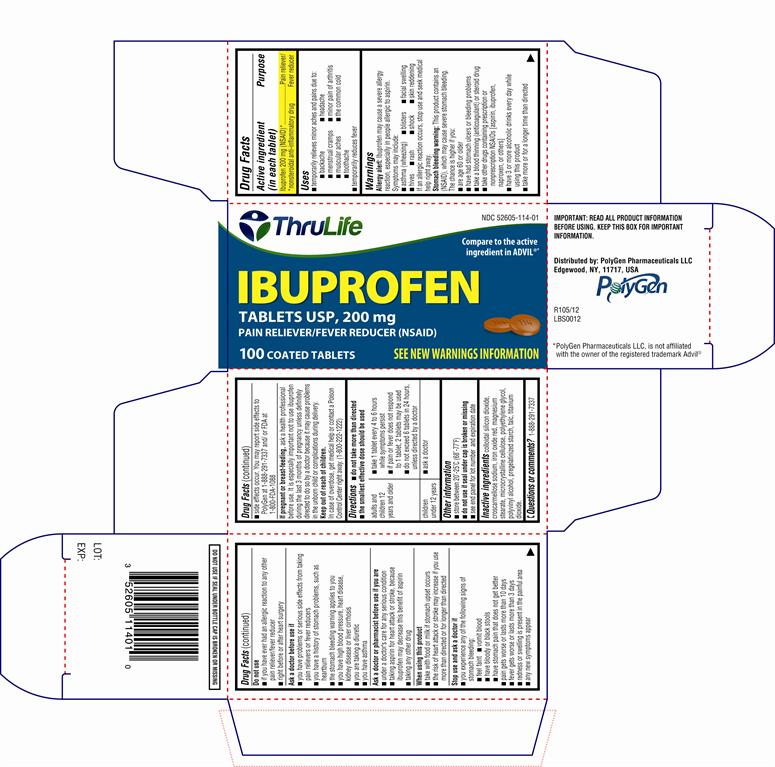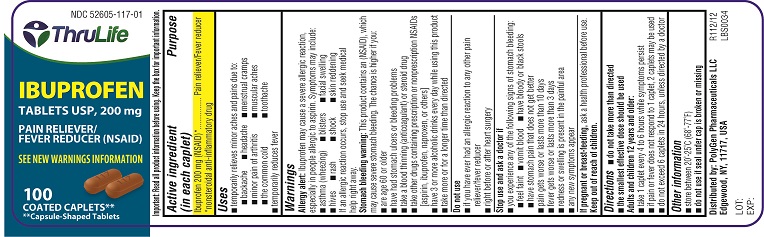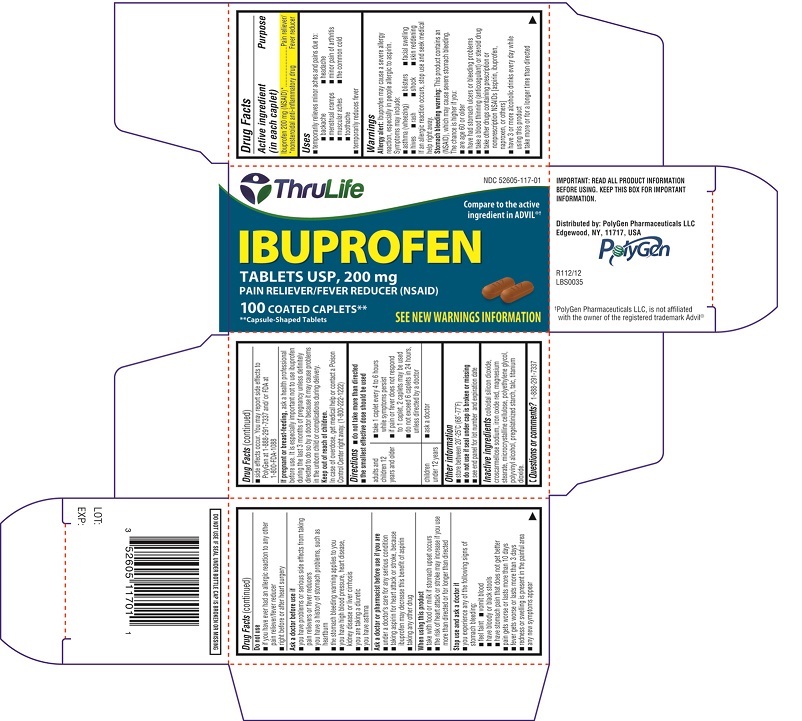 DRUG LABEL: Ibuprofen 
NDC: 52605-114 | Form: TABLET, COATED
Manufacturer: Polygen Pharmaceuticals LLC
Category: otc | Type: Human OTC Drug Label
Date: 20130627

ACTIVE INGREDIENTS: IBUPROFEN 200 mg/1 1
INACTIVE INGREDIENTS: CROSCARMELLOSE SODIUM; COLLOIDAL SILICON DIOXIDE; FERRIC OXIDE RED; MAGNESIUM STEARATE; CELLULOSE, MICROCRYSTALLINE; POLYETHYLENE GLYCOLS; TALC; TITANIUM DIOXIDE; STARCH, CORN; POLYVINYL ALCOHOL

Ibuprofen Tablets, 200 mg

Active ingredient(s)

Ibuprofen 200 mg (NSAID)*

* nonsteroidal anti-inflammatory drug

Purpose

Pain reliever/Fever reducer

Use(s)

temporarily relieves minor aches and pain due to:

- backache
- headache
- menstrual cramps
- minor pain of arthritis
- muscular aches
- the common cold
- toothache
- temporarily reduces fever

Warnings

Allergy alert: Ibuprofen may cause a severe allergy reaction, especially in people allergic to aspirin.

Symptoms may include:

- asthma (wheezing)
- blisters
- facial swelling
- hives
- rash
- shock
- skin reddening

If an allergic reaction occurs, stop use and seek medical help right away.

Stomach bleeding warning: This product contains an NSAID, which may cause stomach bleeding. The chance is higher if you:

- are age 60 or older
- have had stomach ulcers or bleeding problems
- take a blood thinning (anticoagulant) or steroid drug
- take other drugs containing prescription or non prescription NSAIDs (aspirin, ibuprofen, naproxen, or others)
- have 3 or more alcoholic drinks every day while using this product
- the more or for a longer time than directed

Do not use

- if you have ever had an allergic reaction to any other pain reliever/fever reducer
- right before or after heart surgery

Ask a doctor before use if

- you have problems or serious side effects from taking pain relievers or fever reducers
- you have a history of stomach problems such as heartburn
- the stomach bleeding warning applies to you
- you have high blood pressure, heart disease , kidney disease, liver cirrhosis
- you are taking a diuretic
- you have asthma

Ask a doctor or pharmacist before use if

- under a doctor’s care for any serious condition
- taking aspirin for heart attack or stroke, because ibuprofen may decrease this benefit of aspirin
- taking any other drug

When using this product

- take with food or milk if stomach upset occurs
- the risk of heart attack or stroke may increase if you use more than directed or for longer than directed

Stop use and ask doctor if

- you experience any of the following signs of stomach bleeding: ● feel faint ●vomit blood● have bloody or black stools ● have stomach pain that does not get better
- pain gets worse or lasts more than 10 days
- fever gets worse or lasts more than 3 days
- redness or swelling is present in the painful area
- any new symptoms occur

Side effects occur. You may report side effects to PolyGen at 1-888-291-7337 and/ or FDA at 1-800-FDA-1088

Pregnancy/Breastfeeding

ask a health professional before use. It is especially important not to use ibuprofen during the last 3 months of pregnancy unless definitely directed to do so by a doctor because it may cause problems in the unborn child or complications during delivery.

Keep out of reach of children

In case of overdose, get medical help or contact a Poison Control Center right away. (1-800-222-1222)

Directions

- do not take more than directed
- the smallest effective dose should be used

adults and children 12 years and older: | · take 1 tablet every 4 to 6 hours while symptoms persist · if pain or fever does not respond to 1 tablet, 2 tablets may be used · do not exceed 6 tablets in 24 hours unless directed by a doctor
children under 12 years: | ask a doctor

other information

- do not use if seal under cap is broken or missing
- see end panel for lot number and expiration date

Inactive ingredient

colloidal silicon dioxide, croscarmellose sodium, iron oxide red, magnesium stearate, microcrystalline cellulose, polyethylene glycol, polyvinyl alcohol, pregelatinized starch, talc, titanium dioxide

Storage

- store between 20-25 °C (68-77 ° F).

Questions

1-888-291-7337

Principal Display Panel

CARTON LABEL PDP

NDC: 52605-114-01

Compare to the active ingredient in Advil®

IBUPROFEN TABLETS, USP 200 mg

PAIN RELIEVER/ FEVER REDUCER (NSAID)

100 COATED TABLETS

SEE NEW WARNINGS INFORMATION

BOTTLE LABEL PDP

NDC: 52605-114-01

IBUPROFEN TABLETS, USP 200 mg

PAIN RELIEVER/ FEVER REDUCER(NSAID)

100 COATED TABLETS

SEE NEW WARNINGS INFORMATION

CARTON LABEL PDP

NDC: 52605-117-01

Compare to the active ingredient in Advil®

IBUPROFEN TABLETS, USP 200 mg

PAIN RELIEVER/ FEVER REDUCER (NSAID)

100 COATED CAPLETS

SEE NEW WARNINGS INFORMATION

BOTTLE LABEL PDP

NDC: 52605-117-01

IBUPROFEN TABLETS, USP 200 mg

PAIN RELIEVER/ FEVER REDUCER(NSAID)

100 COATED CAPLETS

SEE NEW WARNINGS INFORMATION